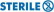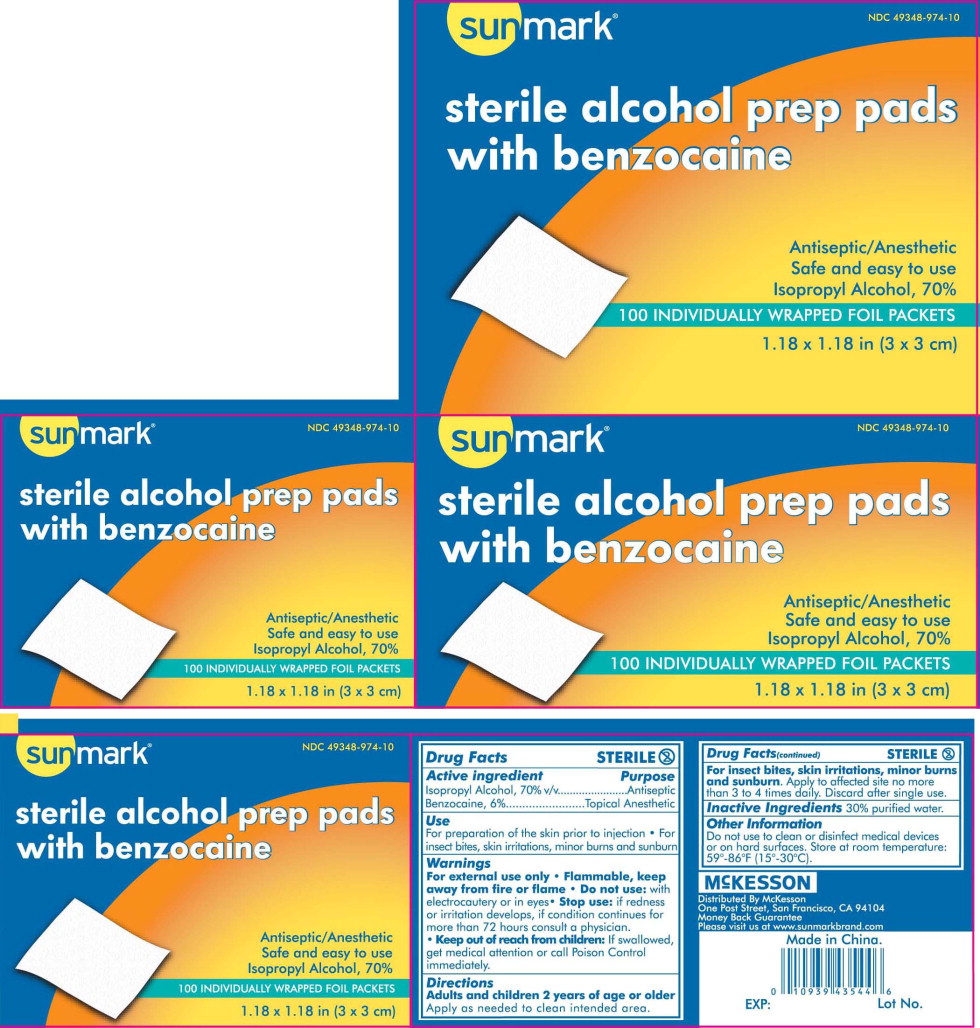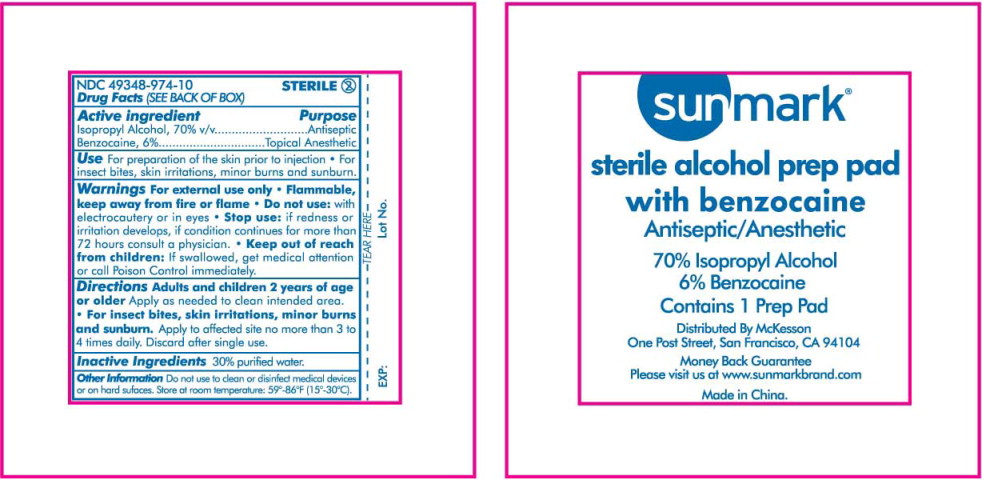 DRUG LABEL: Isopropyl Alcohol with Benzocaine
NDC: 49348-974 | Form: SWAB
Manufacturer: McKesson Corporation
Category: otc | Type: HUMAN OTC DRUG LABEL
Date: 20120601

ACTIVE INGREDIENTS: Isopropyl Alcohol 0.7 mL/1 mL; Benzocaine 0.06 mL/1 mL
INACTIVE INGREDIENTS: Water

Drug Facts

Active ingredient

Isopropyl Alcohol, 70% v/v

Benzocaine, 6%

Purpose

Antiseptic

Topical Anesthetic

Use

For preparation of the skin prior to injection

- For insect bites, skin irritations, minor burns and sunburn

Warnings

For external use only

- Flammable, keep away from fire or flame

- Do not use: with electrocautery or in eyes

- Stop use: if redness or irritation develops, if condition continues for more than 72 hours consult a physician.

KEEP OUT OF REACH OF CHILDREN

- Keep out of reach from children: If swallowed, get medical attention or call Poison Control immediately.

Directions

Adults and children 2 years of age or older Apply as needed to clean intended area.

For insect bites, skin irritations, minor burns and sunburn. Apply to affected site no more than 3 to 4 times daily. Discard after single use.

Inactive Ingredients

30% purified water.

Other Information

Do not use to clean or disinfect medical devices or on hard surfaces. Store at room temperature: 59°-86°F (15°-30°C).

Mc KESSON

Distribute By McKesson
One Post Street, San Francisco, CA 94104
Money Back Guarantee
Please visit us at www.sunmarkbrand.com

Principal Display Panel – Box Label

sunmark®

NDC 49348-974-10

sterile alcohol prep pads
with benzocaine
Antiseptic/Anesthetic

Safe and easy to use

70% Isopropyl Alcohol

100 INDIVIDUALLY WRAPPED FOIL PACKETS

1.18 X 1.18 IN (3 X 3 CM)

Principal Display Panel – Packet Label

sunmark®

sterile alcohol prep pad
with benzocaine
Antiseptic/Anesthetic

70% Isopropyl Alcohol
6% Benzocaine

Contains 1 Prep Pad

Distributed By McKesson
One Post Street, San Francisco, CA 94104

Money Back Guarantee
Please visit us at www.sunmarkbrands.com

Made in China